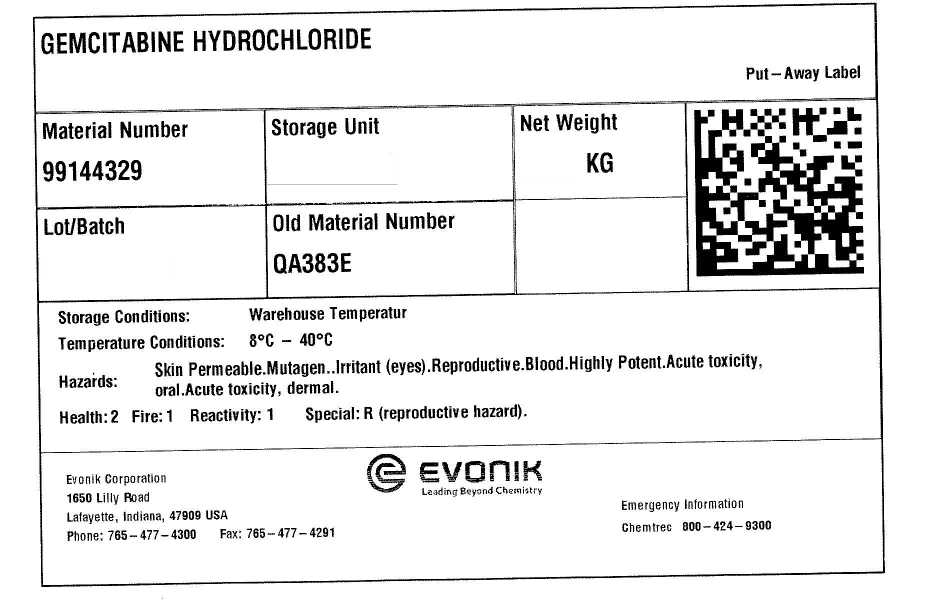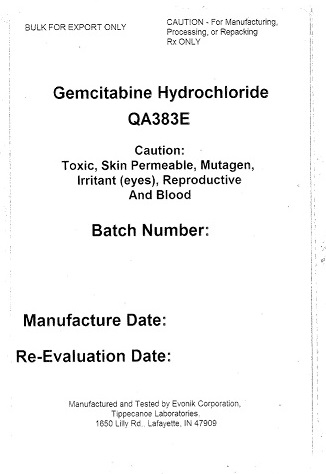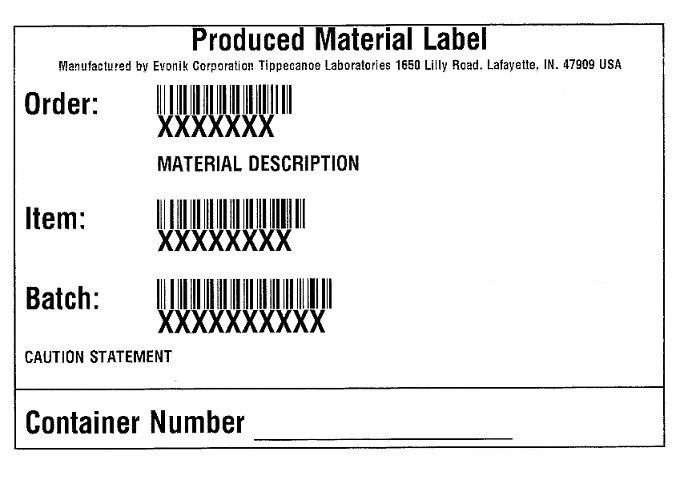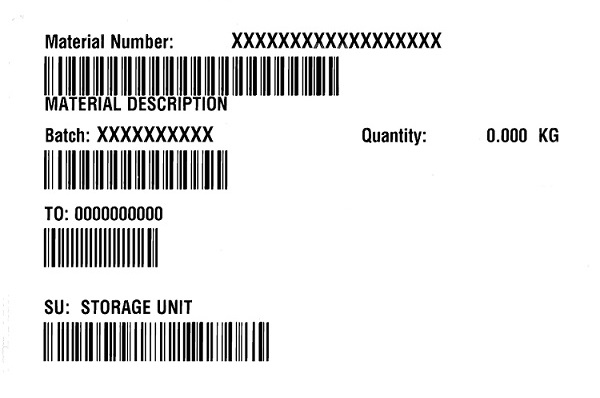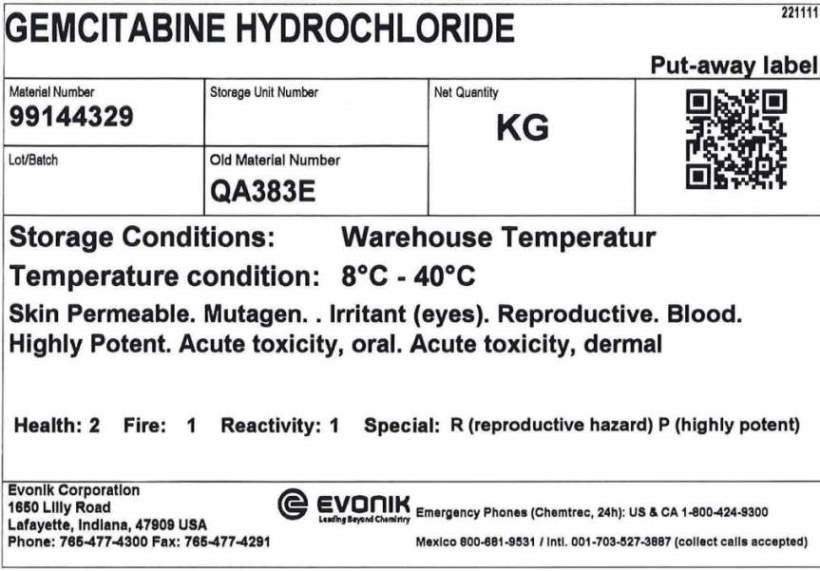 DRUG LABEL: Gemcitabine hydrochloride
NDC: 62128-0383 | Form: POWDER
Manufacturer: Evonik Corporation
Category: other | Type: BULK INGREDIENT
Date: 20250627

ACTIVE INGREDIENTS: GEMCITABINE HYDROCHLORIDE 1 kg/1 kg

Gemcitabine, QA383E

On each inner pail. (Generic) Produced Material Label

For every pail, this label is applied:

Produced Material Label

Manufactured by:

Evonik Corporation Tippecanoe Laboratories

1650 Lilly Road, Lafayette, IN 47909 USA

Order:

Material Description:

Item:

Batch:

Caution statement:

Container number:

Shipping Label on Outer drum.

Bulk for Export Only

Caution: For Manufacturing, processing or repacking. Rx Only.

Gemcitabine hydrochloride

QA383E

Caution: Toxic, skin permeable, mutagen, irritant (eyes), reproductive, and blood.

Batch number:

Manufacture date:

Re-evaluation date:

Manufactured and tested by Evonik Corporation, Tippecanoe Laboratories, 1650 Lilly Road, Lafayette, IN 47909

(generic) Warehouse weight label

As the drum is weighed in the warehouse, this label is applied with the net weight and storage location:

Material number:

Material description:

Batch:

TO:

SU: Storage unit

Quantity: kg

May 2022 Warehouse KG label

Gemcitabine Hydrochloride

Put-Away Label

Material Number 99144329

Storage Unit

Net Weight xx Kg

Lot/Batch

Old Material Number QA383E

QR code box

Storage Conditions: Warehouse temperature

Temperature Conditions: 8 to 40°C

Hazards:

Skin permeable. Mutagen. Irritant (eyes). Reproductive. Blood. Highly potent.

Acute toxicity, oral. Acute toxicity, dermal.

Health 2

Fire 1

Reactivity 1

Special R (reproductive hazard)

Evonik Corporation

1650 Lilly Road Lafayette, Indiana 47909 USA

Phone: 765-477-4300 Fax: 765-477-4291

Evonik: Leading beyond Chemistry

Emergency Information: Chemtrec 800-424-9300

Warehouse KG ELMa Dec2022

Gemcitabine Hydrochloride

Put-away label

Material number: 99144329

Storage unit number

Net quantity: KG

QR Code

Lot/Batch number:

Old Material Number: QA383E

Storage Conditions: Warehouse Temperatur

Temperature condition: 8°C to 40°C

Skin permeable. Mutagen. Irritant (eyes). Reproductive. Blood.

Highly potent. Acute toxicity, oral. Acute toxicity, dermal.

Health: 2

Fire: 1

Reactivity: 1

Special: R (reproductive hazard) P (highly potent)

Evonik Corporation

1650 Lilly Road

Lafayette, Indiana 47909 USA

Phone: 765-477-4300

Fax: 765-477-4291

Evonik: Leading Beyond Chemistry

Emergency Phones (Chemtrec, 24 h)

US & CA 1-800-424-9300

Mexico 800-681-9531

Intl. 001-703-527-3887 (collect calls accepted)